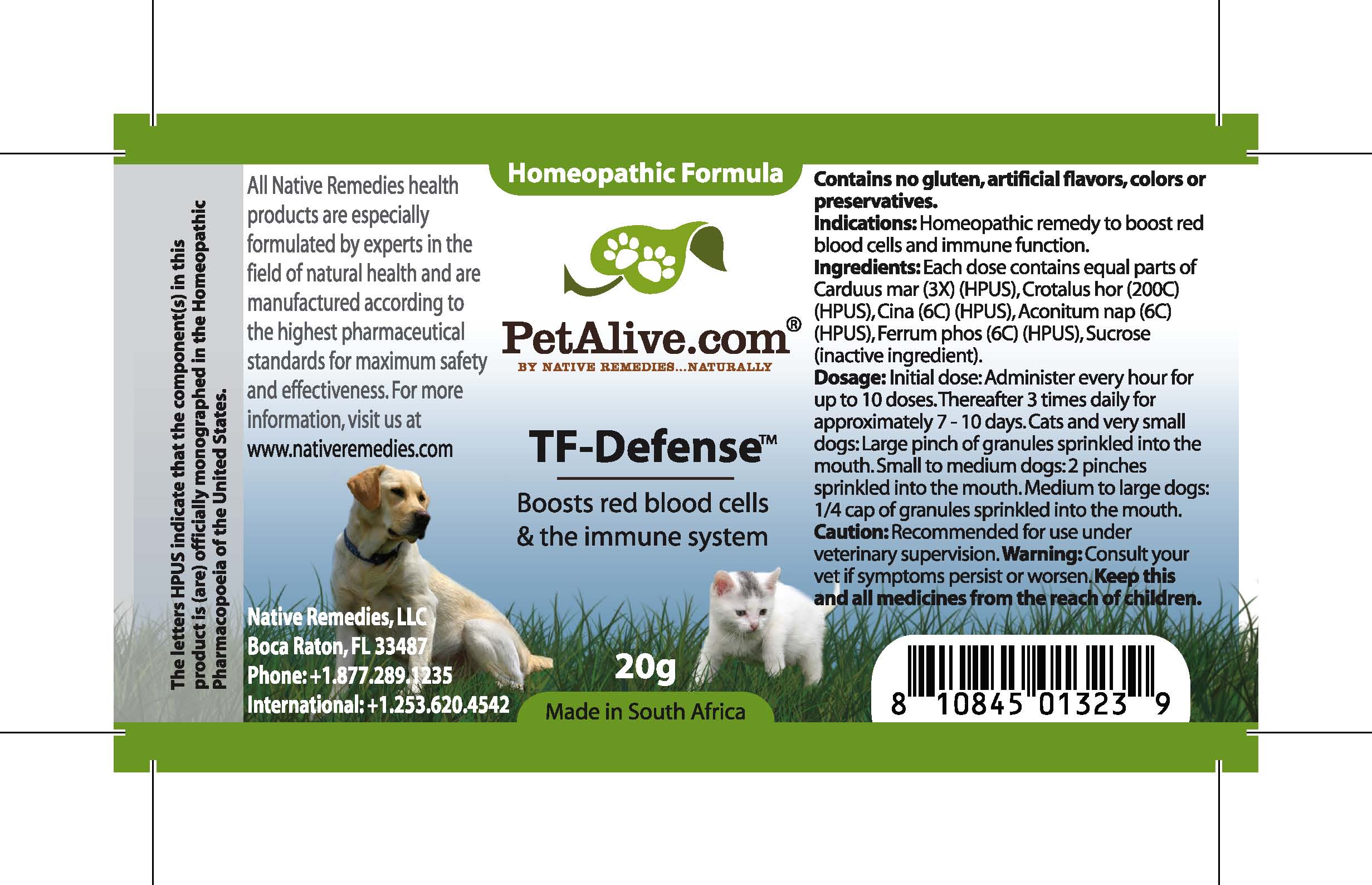 DRUG LABEL: TF Defense
NDC: 68647-151 | Form: GRANULE
Manufacturer: Feelgood Health
Category: homeopathic | Type: OTC ANIMAL DRUG LABEL
Date: 20100917

ACTIVE INGREDIENTS: SILYBUM MARIANUM SEED 3 [hp_X]/40 mg; CROTALUS HORRIDUS HORRIDUS VENOM 200 [hp_C]/40 mg; ARTEMISIA CINA FLOWER 6 [hp_C]/40 mg; ACONITUM NAPELLUS 6 [hp_C]/40 mg; FERRUM PHOSPHORICUM 6 [hp_C]/40 mg
INACTIVE INGREDIENTS: SUCROSE 20000 mg/20000 mg

TF DEFENSE

PURPOSE

Boosts red blood cells and the immune system

INDICATIONS AND USAGE

Indications: Homeopathic remedy to boost red blood cells and immune function.

DOSAGE AND ADMINISTRATION

Dosage: Initial dose: Administer every hour for up to 10 doses. Thereafter 3 times daily for approximately 7-10 days. Cats and dogs under 20 lbs: Large pinch of granules sprinkled into the mouth. Dogs 20-50 lbs: 2 pinches sprinkled into the mouth. Dogs over 50 lbs:1/4 cap of granules sprinkled into the mouth.

GENERAL PRECAUTIONS

Caution: Recommended for use under veterinary supervision. Consult your vet if symptoms persist or worsen. Keep this and all medicines from the reach of children.

ACTIVE INGREDIENT

Ingredients: Each dose contains equal parts of Carduus mar (3X) (HPUS), Crotalus hor (200C) (HPUS), Cina (6C) (HPUS), Aconitum nap (6C) (HPUS), Ferrum phos (6C) (HPUS)

Sucrose (inactive ingredient).

WARNINGS

Contains no gluten, artificial flavors, colors or preservatives.

PATIENT COUNSELING INFORMATION

All Native Remedies health products are especially formulated by experts in the field of natural health and are manufactured according to the highest pharmaceutical standards for maximum safety and effectiveness. For more information, visit us at www.petalive.com

Distributed by

Native Remedies, LLC

6531 Park of Commerce Blvd.

Suite 160

Boca Raton, FL 33487

Phone: 1.877.289.1235

International: + 1.561.999.8857

The letters HPUS indicate that the component(s) in this product is (are) officially monographed in the Homeopathic Pharmacopoeia of the United States.

KEEP OUT OF REACH OF CHILDREN

Keep this and all medicines from the reach of children.